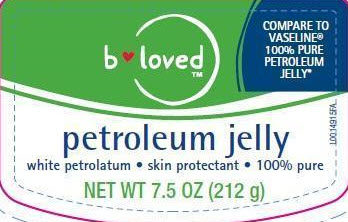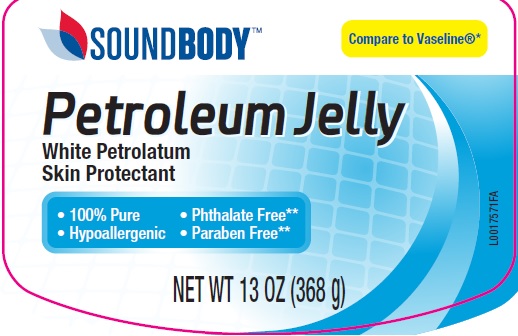 DRUG LABEL: Petroleum
NDC: 50594-069 | Form: JELLY
Manufacturer: Big Lots Stores, Inc.
Category: otc | Type: HUMAN OTC DRUG LABEL
Date: 20260129

ACTIVE INGREDIENTS: PETROLATUM 1 g/1 g

Sound Body_B Loved 069.001/069AA
Petroleum Jelly

Active ingredient

White petrolatum USP (100%)

Purpose

Skin Protectant

Uses

- temporarily protects minor: -cuts -scrapes -burns
- temporarily protects and helps relieve chapped or cracked skin and lips
- helps protect from the drying effects of wind and cold weather

Warnings

For external use only

When using this product

- do not get into eyes

See doctor if

condition lasts more than 7 days

Do not use on

- deep or puncture wounds
- animal bites
- serious burns

Keep out of reach of children.

If swallowed, get medical help or contact a Poison Control Center right away.

Directions

apply as needed

Inactive ingredients

None

Disclaimer

*This product is not manufactured or distributed by Unilever, distributor of Vaseline®

**Parabens and Phthalates are not normally in this product.

ADVERSE REACTION

Manufactured for Big Lots

By: Vi-Jon, LLC

8515 Page Avenue

St. Louis, MO 63114

PRINCIPAL DISPLAY PANEL

SOUNDBODY

Compare to Vaseline*

Petroleum Jelly

White Petrolatum

Skin Protectant

- 100% Pure
- Hypoallergenic
- Phthalate free**
- Paraben free**

NET WT 13 oz (368 g)

PRINCIPAL DISPLAY PANEL

b loved™

COMPARE TO VASELINE®100% PURE PETROLEUM JELLY*

petroleum jelly

white petroleum • skin protectant • 100% pure

NET WT 7.5 OZ (212 g)